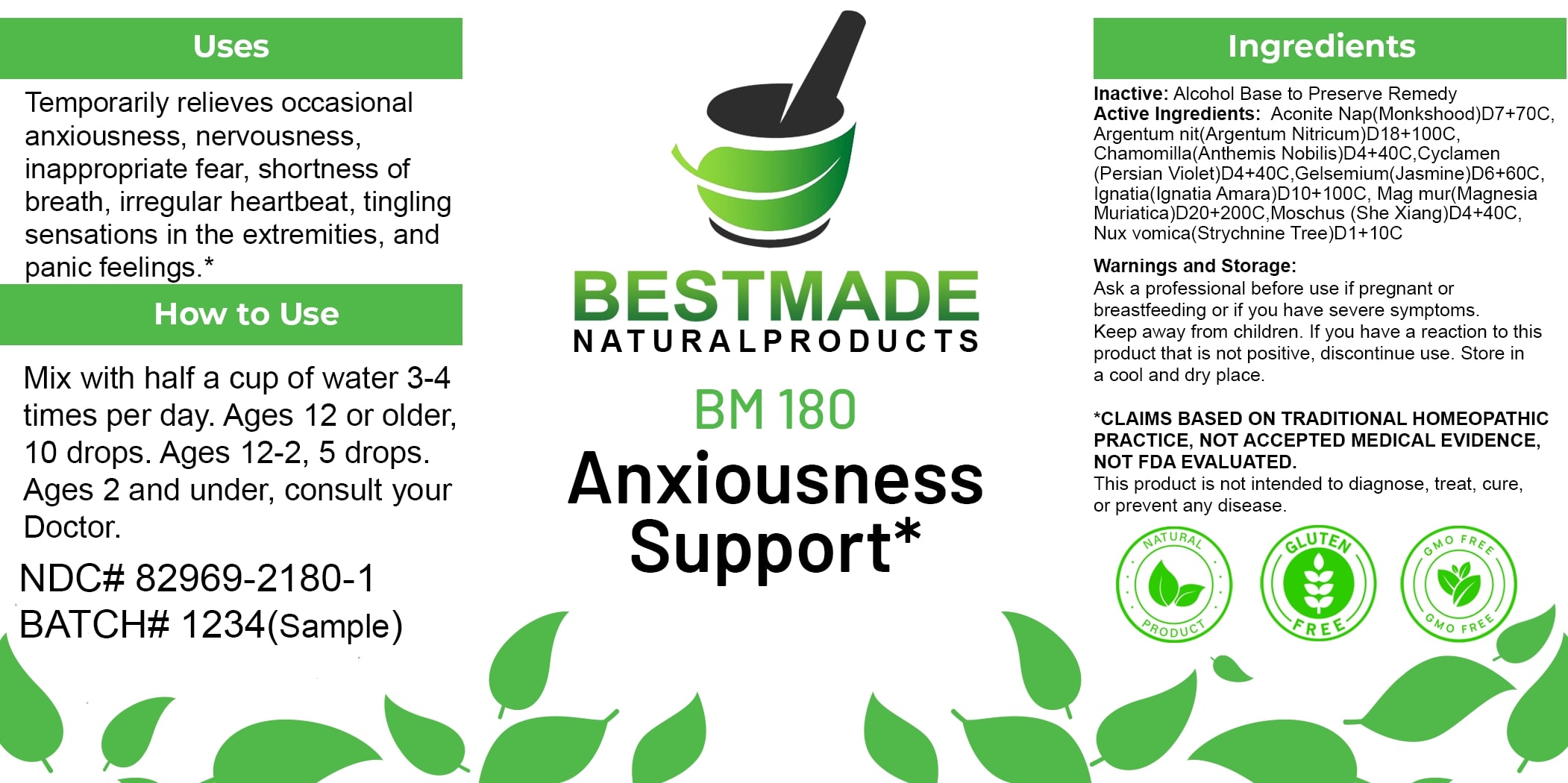 DRUG LABEL: Bestmade Natural Products BM180
NDC: 82969-2180 | Form: LIQUID
Manufacturer: Bestmade Natural Products
Category: homeopathic | Type: HUMAN OTC DRUG LABEL
Date: 20250219

ACTIVE INGREDIENTS: ACONITUM NAPELLUS 30 [hp_C]/30 [hp_C]; MAGNESIUM CHLORIDE 30 [hp_C]/30 [hp_C]; STRYCHNOS IGNATII SEED 30 [hp_C]/30 [hp_C]; MOSCHUS MOSCHIFERUS MUSK SAC RESIN 30 [hp_C]/30 [hp_C]; MATRICARIA CHAMOMILLA 30 [hp_C]/30 [hp_C]; GELSEMIUM SEMPERVIRENS ROOT 30 [hp_C]/30 [hp_C]; SILVER NITRATE 30 [hp_C]/30 [hp_C]; STRYCHNOS NUX-VOMICA SEED 30 [hp_C]/30 [hp_C]; CYCLAMEN PURPURASCENS TUBER 30 [hp_C]/30 [hp_C]
INACTIVE INGREDIENTS: ALCOHOL 30 [hp_C]/30 [hp_C]

BM180

DOSAGE AND ADMINISTRATION

How to Use

Mix with half a cup of water 3-4 times per day. Ages 12 or older, 10 drops. Ages 12-2, 5 drops. Ages 2 and under, consult your Doctor.

INACTIVE INGREDIENT

Ingredients

Inactive: Alcohol Base to Preserve Remedy

ACTIVE INGREDIENT

Active Ingredients: Aconite Nap(Monkshood)D7+70C, Argentum Nit(Argentum Nitricum)D18+100C, Chamomilla(Anthemis Nobilis)D4+40C, Cyclamen (Persian Violet)D4+40C, Gelsemium(Jasmine)D6+60C, Ignatia(Ignatia Amara)D10+100C, Mag mur(Magnesia Muriatica)D20+200C, Moschus (She Xiang)D4+40C, Nux vomica(Strychnine Tree)D1+10C

Uses

Temporarily relieves occasional anxiousness, nervousness, inappropriate fear, shortness of breath, irregular heartbeat, tingling sensations in the extremities, and panic feelings.*

*CLAIMS BASED ON TRADITIONAL HOMEOPATHIC PRACTICE, NOT ACCEPTED MEDICAL EVIDENCE. NOT FDA EVALUATED.

This product is not intended to diagnose, treat, cure, or prevent any disease.

Uses

Temporarily relieves occasional anxiousness, nervousness, inappropriate fear, shortness of breath, irregular heartbeat, tingling sensations in the extremities, and panic feelings.*

*CLAIMS BASED ON TRADITIONAL HOMEOPATHIC PRACTICE, NOT ACCEPTED MEDICAL EVIDENCE. NOT FDA EVALUATED.

This product is not intended to diagnose, treat, cure, or prevent any disease.

KEEP OUT OF REACH OF CHILDREN

Warnings and Storage:

Ask a professional before use if pregnant or breastfeeding or if you have severe symptoms. Keep away from children. If you have a reaction to this product that is not positive, discontinue use. Store in a cool and dry place.

Warnings and Storage:

Ask a professional before use if pregnant or breastfeeding or if you have severe symptoms. Keep away from children. If you have a reaction to this product that is not positive, discontinue use. Store in a cool and dry place.

*CLAIMS BASED ON TRADITIONAL HOMEOPATHIC PRACTICE, NOT ACCEPTED MEDICAL EVIDENCE. NOT FDA EVALUATED.

This product is not intended to diagnose, treat, cure, or prevent any disease.

Entire package label